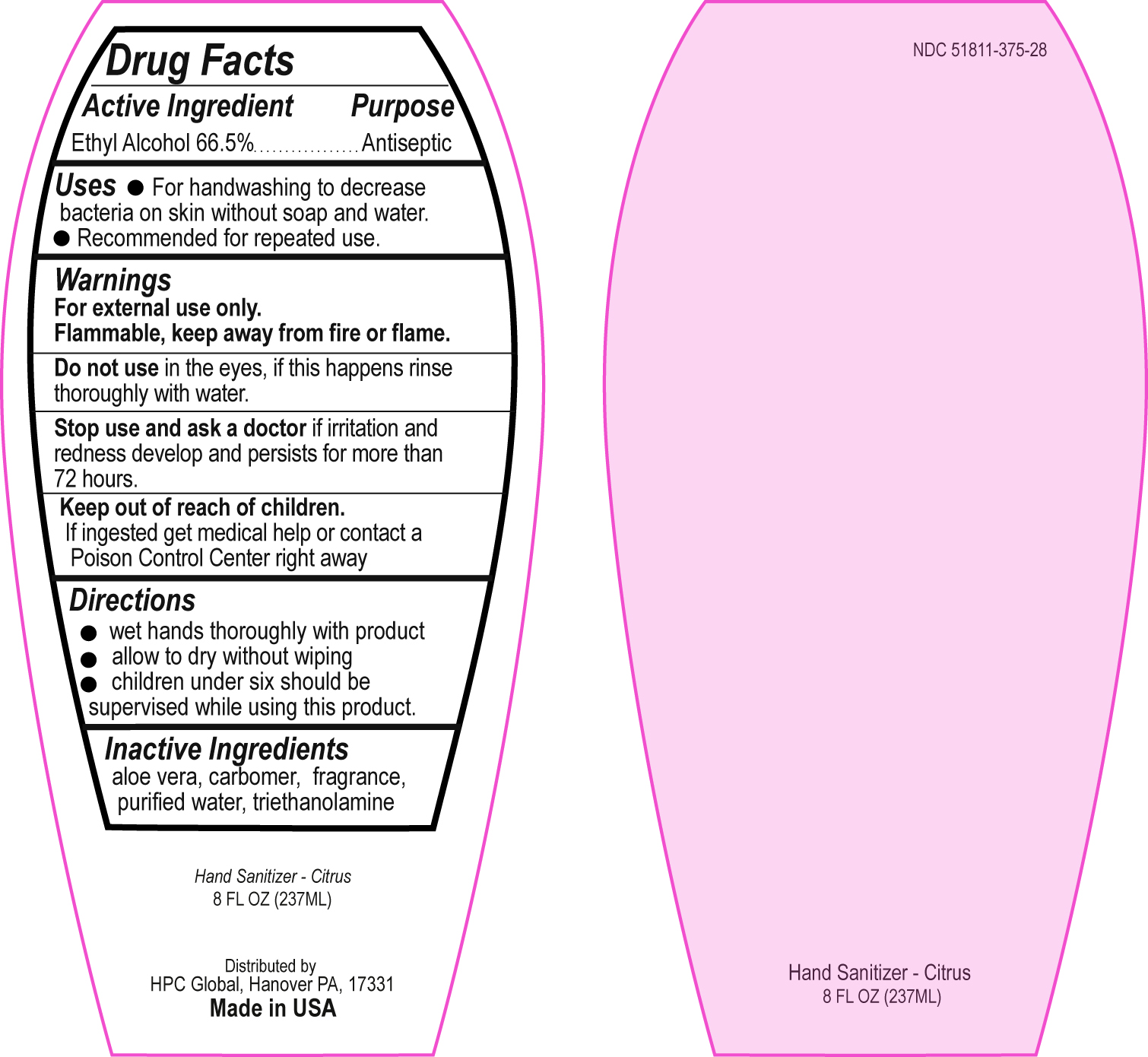 DRUG LABEL: Hand Sanitizer
NDC: 51811-375 | Form: GEL
Manufacturer: Hanover Pen Corp dba HPC Global
Category: otc | Type: HUMAN OTC DRUG LABEL
Date: 20120412

ACTIVE INGREDIENTS: Alcohol 0.665 g/1 mL
INACTIVE INGREDIENTS: Trolamine; Aloe; Water

Drug Facts

Active Ingredient

Ethyl Alcohol 66.5%

Purpose

Antiseptic

Uses

For handwashing to decrease bacteria on skin without soap and water.

Recommended for repeated use.

Warnings

For external use only.

Flammable, keep away from fire or flame.

Do not use in the eyes. If this happens rinse throughly with water

Stop use and ask a doctor if irritation and redness develop and persists for more than 72 hours.

Keep out of reach of children

If ingested get medical help or contact a Poison Control Center right away.

Directions

wet hands throughly with product

allow to dry without wiping

children under six should be supervised while using this produce.

Inactive Ingredients

aloe vera, carbomer, fragrance, purified water, triethanolamine

PACKAGE LABEL PRINCIPAL DISPLAY PANEL

Front Label

NDC 51811-375-28

Hand Sanitizer - Citrus

8 FL oz (237ML)

Back Label (Drug Facts)

Hand Sanitizer - Citrus

8 FL oz (237ML)

Distributed by

HPC Global, Hanover PA, 17331

Made in USA